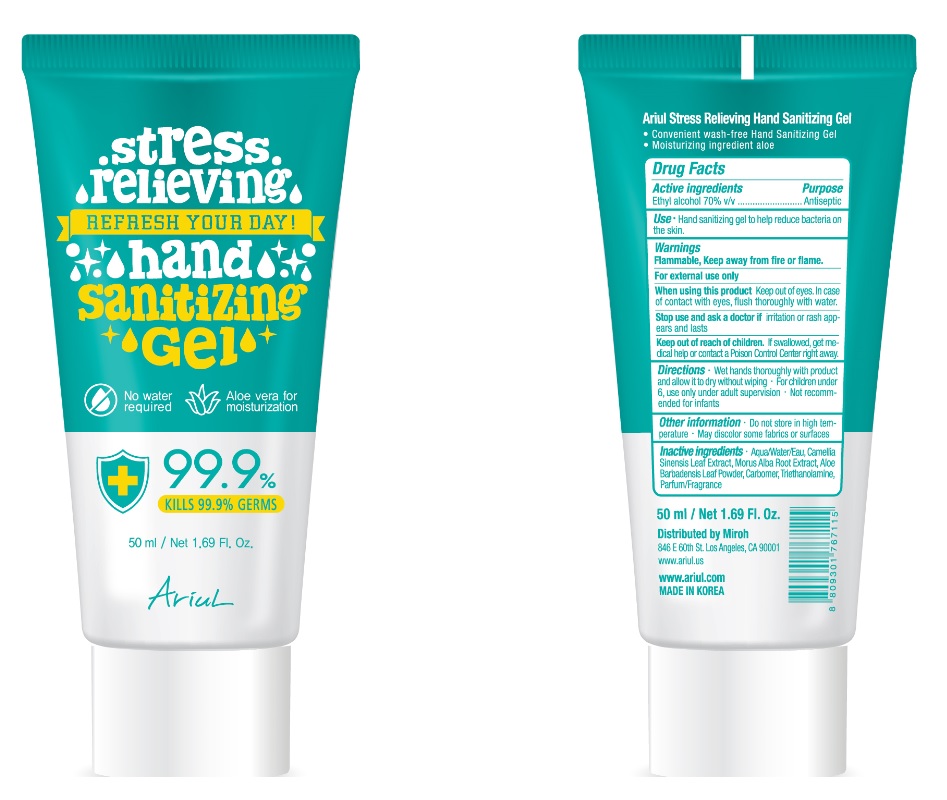 DRUG LABEL: Ariul Stress Relieving Hand Sanitizing Gel
NDC: 77416-750 | Form: GEL
Manufacturer: Beauty Factory Co., Ltd.
Category: otc | Type: HUMAN OTC DRUG LABEL
Date: 20200505

ACTIVE INGREDIENTS: ALCOHOL 35 mL/50 mL
INACTIVE INGREDIENTS: GREEN TEA LEAF; MORUS ALBA ROOT; ALOE VERA LEAF; CARBOMER HOMOPOLYMER, UNSPECIFIED TYPE; WATER; TROLAMINE

[Ariul Stress Relieving Hand Sanitizing Gel] 50 ml : 77416-750-01